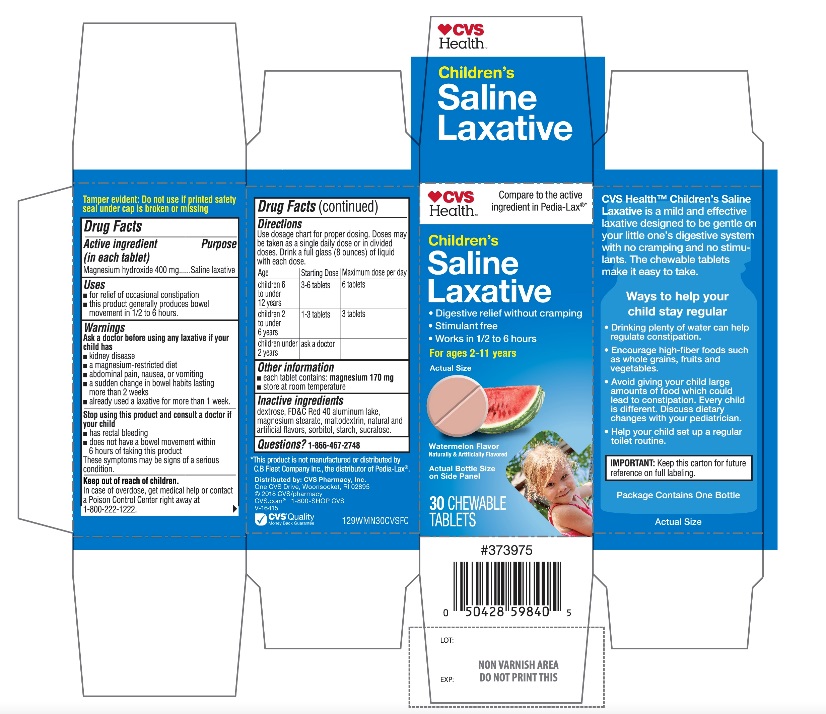 DRUG LABEL: CVS Health Childrens

NDC: 69842-912 | Form: TABLET, CHEWABLE
Manufacturer: CVS PHARMACY,INC.
Category: otc | Type: HUMAN OTC DRUG LABEL
Date: 20251208

ACTIVE INGREDIENTS: MAGNESIUM HYDROXIDE 400 mg/1 1
INACTIVE INGREDIENTS: DEXTROSE, UNSPECIFIED FORM; FD&C RED NO. 40; MAGNESIUM STEARATE; MALTODEXTRIN; SORBITOL; STARCH, CORN; SUCRALOSE

CVS Health Children’s Saline Laxative 30 Chewable Tablets

Active Ingredient

Magnesium hydroxide 400 mg

Purpose

Saline laxative

Uses

- for relief of occasional constipation
- this product usually produces bowel movement in 1/2 to 6 hours

Warnings

Ask a doctor before using any laxative if child has

- kidney disease
- a magnesium-restricted diet
- abdominal pain, nausea or vomiting
- a sudden change in bowel habits lasting more than 2 weeks
- already used a laxative for more than 1 week

Stop use and consult a doctor if your child has

- has rectal bleeding
- does not have a bowel movement within 6 hours of taking this product

These symptoms may indicate a serious condition.

Keep out of reach of children

In case of overdose, get medical help or contact a Poison Control Center right away at 1-800-222-1222.

Directions

Use dosage chart for proper dosing. Doses may be taken as a single daily dose or in divided doses. Drink a full glass (8 ounces) of liquid with each dose.

Age | Starting dose | Maximum dose per day
children 6 to under 12 years | 3-6 tablets | 6 tablets
children 2 to under 6 years | 1-3 tablets | 3 tablets
children under 2 years | ask a doctor

Other information

- each tablet contains: magnesium 170 mg
- store at room temperature

Inactive ingredients

dextrose, FD&C Red 40 aluminum lake, magnesium stearate, maltodextrin, natural and artificial flavor, sorbitol, starch, sucralose.

Questions or comments?

1-866-467-2748

PRINCIPAL DISPLAY PANEL

CVS Health™

Compare to the active ingredientPedia-Lax®*

NDC# 69842-912-30

Children’s

Saline Laxative

- Digestive relief without cramping
- Stimulant-free
- Works in ½ to 6 hours

For ages 2-11 years

Watermelon Flavor

Naturally and Artificially Flavor

30 CHEWABLE TABLETS

CVS Health™ Children’s Saline Laxative is a mild and effective laxative designed to be gentle on your little one’s digestive system with no cramping and no stimulants. The chewable tablets make it easy to take.

IMPORTANT:Keep this carton for future reference on full labeling.

*This product is not manufactured or distributed by C.B Fleet Company Inc., the distributor of Pedia-Lax®

Distributed by: CVS Pharmacy, Inc.

One CVS Drive, Woonsocket, RI 02895

© 2018 CVS/pharmacy

CVS.com 1-800-SHOP CVS

V-16415

CVS®Quality

Money Back Guarantee